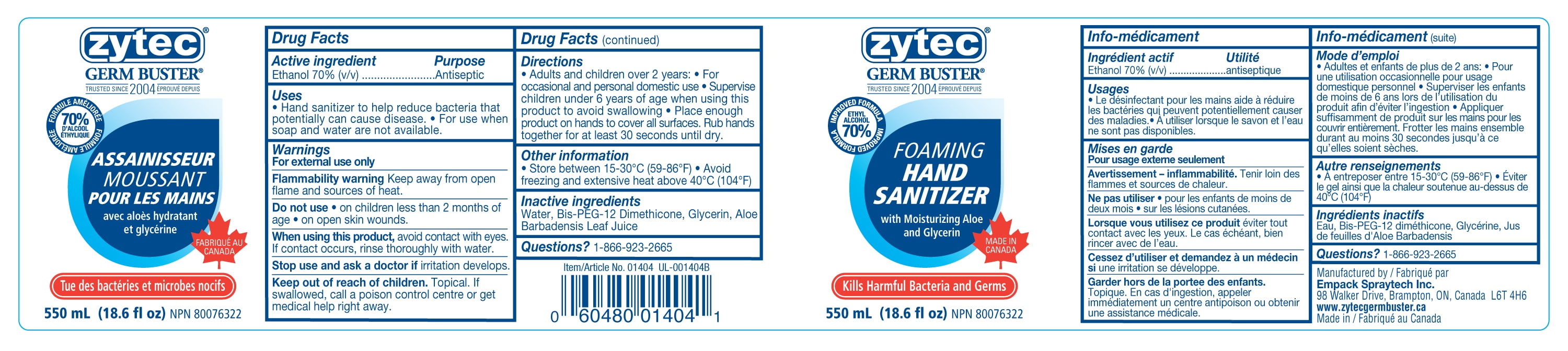 DRUG LABEL: Foaming Hand Sanitizer
NDC: 50021-020 | Form: SOLUTION
Manufacturer: Empack Spraytech Inc.
Category: otc | Type: HUMAN OTC DRUG LABEL
Date: 20241212

ACTIVE INGREDIENTS: ALCOHOL 70 mL/100 mL
INACTIVE INGREDIENTS: GLYCERIN; BIS-PEG-12 DIMETHICONE (500 MPA.S); WATER; ALOE VERA LEAF

50021-020 Foaming Hand Sanitizer

Active Ingredient(s)

Ethanol 70% (v/v)

Purpose

Antiseptic

Uses

Hand sanitizer to help reduce bacteria that potentially can cause disease. For use whensoap and water are not available.

Warnings

For external use only. Flammability warning. Keep away from open flame and sources of heat.

Do not use

- on children less than 2 months of age
- on open skin wounds

When using this product,avoid contact with eyes. If contact occurs, rinse thoroughly with water.

Stop use and ask a doctor ifirritation develops.

Keep out of reach of children.Topical. If swallowed, call a poison control centre or get medical help right away.

Directions

- Adults and children over 2 years
- For occasional and personal domestic use
- Supervise children under 6 years of age when using this product to avoid swallowing
- Place enough product on hands to cover all surfaces. Rub hands together for at least 30 seconds until dry.

Other information

- Store between 15-30C (59-86F)
- Avoid freezing and excessive heat above 40C (104F)

Inactive ingredients

Water, Bis-PEG-12 Dimethicone, Glycerin, Aloe Barbadensis Leaf Juice

Questions?

1-866-923-2665

UPC

Manufactured by Empack Spraytech Inc., 98 Walker Drive, Brampton, ON, Canada L6T 4H6

www.zytecgermbuster.ca

Made in Canada

Lot # and Expiry Date to be embossed on the bottle

Package Label - Principal Display Panel

550 ml; NDC 50021-020-01